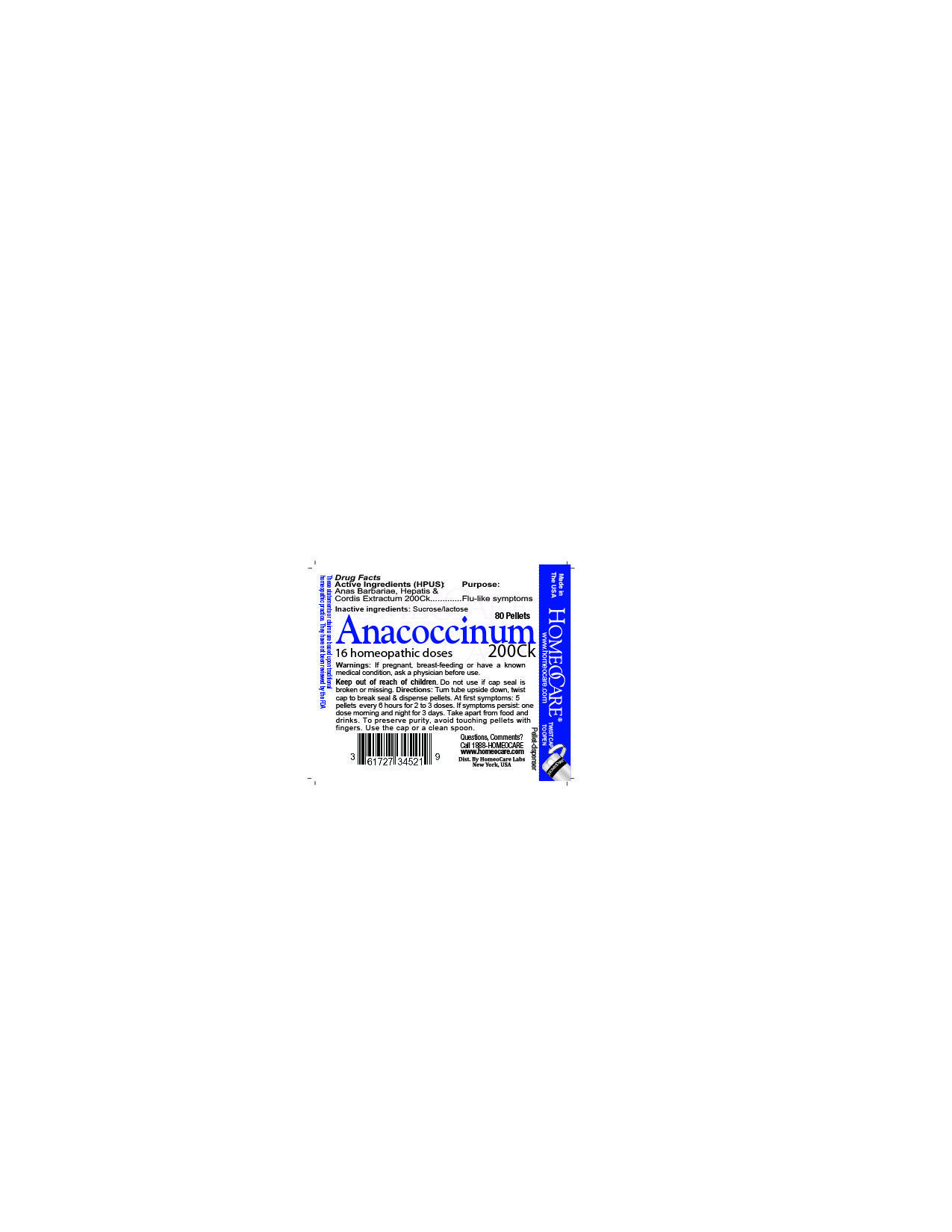 DRUG LABEL: ANACOCCINUM
NDC: 61727-345 | Form: PELLET
Manufacturer: HomeoCare Laboratories
Category: homeopathic | Type: HUMAN OTC DRUG LABEL
Date: 20190320

ACTIVE INGREDIENTS: CAIRINA MOSCHATA HEART/LIVER AUTOLYSATE 200 [hp_C]/1 1
INACTIVE INGREDIENTS: LACTOSE; SUCROSE

ANACOCCINUM

Active ingredient

Anas Barbariae, Hepatis & Cordis Extractum 200Ck.

Directions

Turn tube upside down, twist cap to break seal & dispense pellets. At first symptoms: 5 pellets every 6 hours for 2 to 3 doses. If symptoms persist: one dose morning and night for 3 days. Take apart from food and drinks. To preserve purity, avoid touching pellets with fingers. Use the cap or a clean spoon.

INDICATIONS & USAGE

At first symptoms: 5 pellets every 6 hours for 2 to 3 doses. If symptoms persist: one dose morning and night for 3 days.

ake apart from food and drinks. To preserve purity, avoid touching pellets with
fingers. Use the cap or a clean spoon.

Inactive ingredients

Sucrose, lactose

Purpose

Flu-like symptoms

OTC - KEEP OUT OF REACH OF CHILDREN SECTION

Keep out of reach of children.

Warnings

If pregnant, breast-feeding or have a known medical condition, ask a physician before use

Keep out of the reach of children. Do not use if cap seal is broken or missing.

OTC - PREGNANCY OR BREAST FEEDING SECTION

If pregnant, breast-feeding or have a known medical condition, ask a physician before use.

Anacoccinum 200 Ck label

HCL_label_Anacoccinum 200ck.jpg